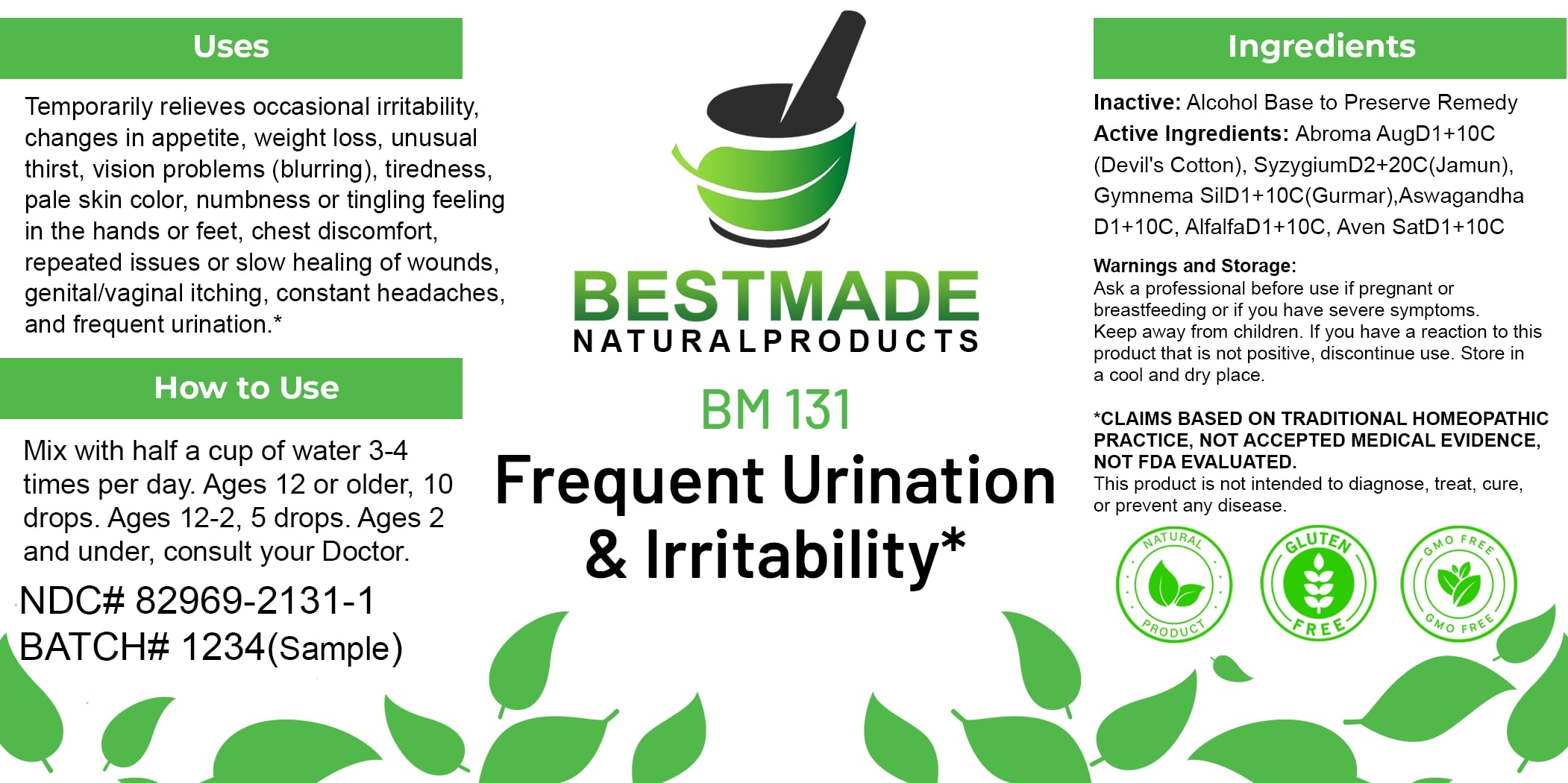 DRUG LABEL: Bestmade Natural Products BM131
NDC: 82969-2131 | Form: LIQUID
Manufacturer: Bestmade Natural Products
Category: homeopathic | Type: HUMAN OTC DRUG LABEL
Date: 20250212

ACTIVE INGREDIENTS: ABROMA AUGUSTUM WHOLE 30 [hp_C]/30 [hp_C]; GYMNEMA SYLVESTRE WHOLE 30 [hp_C]/30 [hp_C]; WITHANIA SOMNIFERA ROOT 30 [hp_C]/30 [hp_C]; SYZYGIUM CUMINI SEED 30 [hp_C]/30 [hp_C]; MEDICAGO SATIVA WHOLE 30 [hp_C]/30 [hp_C]; AVENA SATIVA FLOWERING TOP 30 [hp_C]/30 [hp_C]
INACTIVE INGREDIENTS: ALCOHOL 30 [hp_C]/30 [hp_C]

BM131

DOSAGE AND ADMINISTRATION

How to Use

Mix with half a cup of water 3-4 times per day. Ages 12 or older, 10 drops. Ages 12-2, 5 drops. Ages 2 and under, consult your Doctor.

INACTIVE INGREDIENT

Ingredients

Inactive: Alcohol Base to Preserve Remedy

ACTIVE INGREDIENT

Active Ingredients: Abroma AugD1+10C (Devil's Cotton), SyzygiumD2+20C(Jamun), Gymnema SilD1+10C(Gurmar), Aswagandha D1+10C, AlfalfaD1+10C, Aven SatD1+10C

Uses

Temporarily relieves occasional irritability, changes in appetite, weight loss, unusual thirst, vision problems (blurring), tiredness, pale skin color, numbness or tingling feeling in the hands or feet, chest discomfort, repeated issues or slow healing of wounds, genital/vaginal itching, constant headaches, and frequent urination.*

*CLAIMS BASED ON TRADITIONAL HOMEOPATHIC PRACTICE, NOT ACCEPTED MEDICAL EVIDENCE. NOT FDA EVALUATED.

This product is not intended to diagnose, treat, cure, or prevent any disease.

Uses

Temporarily relieves occasional irritability, changes in appetite, weight loss, unusual thirst, vision problems (blurring), tiredness, pale skin color, numbness or tingling feeling in the hands or feet, chest discomfort, repeated issues or slow healing of wounds, genital/vaginal itching, constant headaches, and frequent urination.*

*CLAIMS BASED ON TRADITIONAL HOMEOPATHIC PRACTICE, NOT ACCEPTED MEDICAL EVIDENCE. NOT FDA EVALUATED.

This product is not intended to diagnose, treat, cure, or prevent any disease.

KEEP OUT OF REACH OF CHILDREN

Warnings and Storage:

Ask a professional before use if pregnant or breastfeeding or if you have severe symptoms. Keep away from children. If you have a reaction to this product that is not positive, discontinue use. Store in a cool and dry place.

Warnings and Storage:

Ask a professional before use if pregnant or breastfeeding or if you have severe symptoms. Keep away from children. If you have a reaction to this product that is not positive, discontinue use. Store in a cool and dry place.

*CLAIMS BASED ON TRADITIONAL HOMEOPATHIC PRACTICE, NOT ACCEPTED MEDICAL EVIDENCE. NOT FDA EVALUATED.

This product is not intended to diagnose, treat, cure, or prevent any disease.

Entire package label